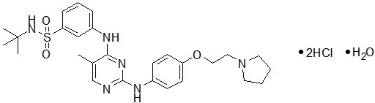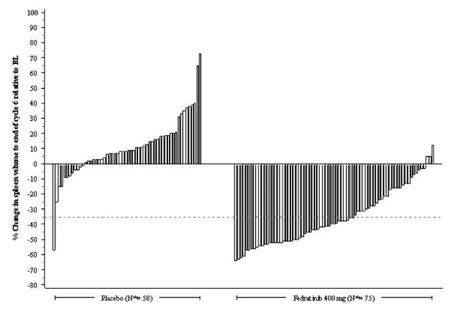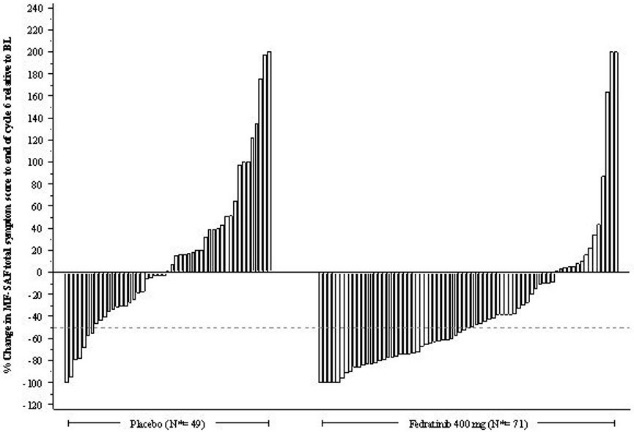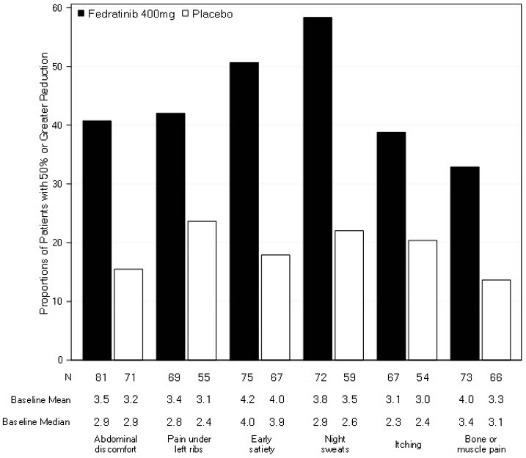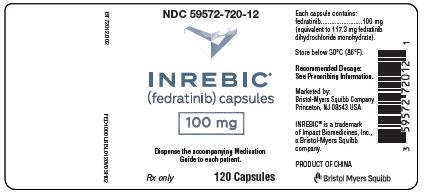 DRUG LABEL: Inrebic
NDC: 59572-720 | Form: CAPSULE
Manufacturer: Celgene Corporation
Category: prescription | Type: HUMAN PRESCRIPTION DRUG LABEL
Date: 20250512

ACTIVE INGREDIENTS: FEDRATINIB HYDROCHLORIDE 100 mg/1 1
INACTIVE INGREDIENTS: SILICON DIOXIDE; MICROCRYSTALLINE CELLULOSE; SODIUM STEARYL FUMARATE; GELATIN, UNSPECIFIED; FERRIC OXIDE RED; TITANIUM DIOXIDE

HIGHLIGHTS OF PRESCRIBING INFORMATION

These highlights do not include all the information needed to use INREBIC safely and effectively. See full prescribing information for INREBIC.
INREBIC® (fedratinib) capsules, for oral use
Initial U.S. Approval: 2019

RECENT MAJOR CHANGES

Boxed Warning | 07/2024
Dosage and Administration (2.1) | 07/2024
Warnings and Precautions (5.1) | 07/2024
Warnings and Precautions (5.6) | 05/2025

WARNING: ENCEPHALOPATHY INCLUDING WERNICKE'S

See full prescribing information for complete boxed warning.

Serious and fatal encephalopathy, including Wernicke's, has occurred in patients treated with INREBIC. Wernicke's encephalopathy is a neurologic emergency. Assess thiamine levels in all patients prior to starting INREBIC. Do not start INREBIC in patients with thiamine deficiency; replete thiamine prior to treatment initiation. While on treatment all patients should receive prophylaxis with daily oral thiamine and should have thiamine levels assessed as clinically indicated. If encephalopathy is suspected, immediately discontinue INREBIC and initiate parenteral thiamine. Monitor until symptoms resolve or improve and thiamine levels normalize. (2.6, 5.1, 6.1).

1 INDICATIONS AND USAGE

INREBIC is a kinase inhibitor indicated for the treatment of adult patients with intermediate-2 or high-risk primary or secondary (post-polycythemia vera or post-essential thrombocythemia) myelofibrosis (MF) (1).

2 DOSAGE AND ADMINISTRATION

- Recommended Dosage: 400 mg orally once daily with or without food for patients with a baseline platelet count of greater than or equal to 50 × 10^9/L (2.2).
- For patients who have difficulty swallowing capsules whole or those with a nasogastric tube, the content of the capsule(s) may be dispersed in Ensure® Plus (2.2).
- Reduce dose for patients taking strong CYP3A inhibitors or with severe renal impairment (2.3, 2.4, 7.1, 8.6).

3 DOSAGE FORMS AND STRENGTHS

Capsules: 100 mg (3).

4 CONTRAINDICATIONS

None.

5 WARNINGS AND PRECAUTIONS

- Anemia and Thrombocytopenia: Manage by dose reduction, interruption, or transfusion (5.2).
- Gastrointestinal Toxicity: Manage by dose reduction or interruption if patient develops severe diarrhea, nausea, or vomiting. Prophylaxis with antiemetics and treatment with antidiarrhea medications are recommended (5.3).
- Hepatic Toxicity: Manage by dose reduction or interruption (5.4).
- Amylase and Lipase Elevation: Manage by dose reduction or interruption (5.5).
- Uveitis: Monitor for symptoms and refer for ophthalmological evaluation (5.6).
- Major Adverse Cardiac Events (MACE): Monitor for development of MACE (5.7).
- Thrombosis: Evaluate and treat symptoms of thrombosis promptly (5.8).
- Secondary Malignancies: Monitor for development of secondary malignancies, particularly in patients who are current or past smokers (5.9).

6 ADVERSE REACTIONS

The most common adverse reactions (≥20%) are diarrhea, nausea, anemia, and vomiting (6.1).

To report SUSPECTED ADVERSE REACTIONS, contact Bristol-Myers Squibb at 1-800-721-5072 or FDA at 1-800-FDA-1088 or www.fda.gov/medwatch.

7 DRUG INTERACTIONS

- Strong CYP3A4 Inhibitors: Reduce INREBIC dose as recommended (2.3, 7.1).
- Strong and Moderate CYP3A4 Inducers: Avoid use of INREBIC (7.1).
- CYP3A4, CYP2C19, or CYP2D6 Substrates: Dose modifications of substrates drugs may be needed (7.2).
- OCT2 and MATE1/2-K Substrates: Dose modifications of substrate drugs may be needed (7.2).

8 USE IN SPECIFIC POPULATIONS

- Lactation: Advise not to breastfeed (8.2).

FULL PRESCRIBING INFORMATION

WARNING: ENCEPHALOPATHY INCLUDING WERNICKE'S

Serious and fatal encephalopathy, including Wernicke's, has occurred in patients treated with INREBIC. Wernicke's encephalopathy is a neurologic emergency. Assess thiamine levels in all patients prior to starting INREBIC. Do not start INREBIC in patients with thiamine deficiency; replete thiamine prior to treatment initiation. While on treatment all patients should receive prophylaxis with daily oral thiamine and should have thiamine levels assessed as clinically indicated. If encephalopathy is suspected, immediately discontinue INREBIC and initiate parenteral thiamine. Monitor until symptoms resolve or improve and thiamine levels normalize [see Dosage and Administration (2.6), Warnings and Precautions (5.1) and Adverse Reactions (6.1)].

1 INDICATIONS AND USAGE

INREBIC® is indicated for the treatment of adult patients with intermediate-2 or high-risk primary or secondary (post-polycythemia vera or post-essential thrombocythemia) myelofibrosis (MF).

2 DOSAGE AND ADMINISTRATION

2.1 Required Concomitant Medications

During treatment with INREBIC, all patients should receive prophylaxis with thiamine 100 mg orally daily [see Dosage and Administration (2.7) and Warnings and Precautions (5.1)].

2.2 Recommended Dosage

Conduct baseline testing of thiamine (Vitamin B1) levels prior to initiation of INREBIC [see Dosage and Administration (2.7), Warnings and Precautions (5.1)].

The recommended dosage of INREBIC is 400 mg taken orally once daily for patients with a baseline platelet count of greater than or equal to 50 × 10^9/L.

Modify the dose for patients using concomitant strong CYP3A4 inhibitors, and in patients with severe renal impairment (creatinine clearance (CLcr) 15 mL/min to 29 mL/min) [see Dosage and Administration (2.4, 2.5)].

Patients that are on treatment with ruxolitinib before the initiation of INREBIC must taper and discontinue according to the ruxolitinib prescribing information.

Administration Information:

- INREBIC may be taken with or without food. Administration with a high fat meal may reduce the incidence of nausea and vomiting.
- If a dose of INREBIC is missed, the next scheduled dose should be taken the following day.
- For patients who have difficulty swallowing capsule(s) whole or those with a nasogastric tube:
- Open the capsule(s).
- In a glass container, mix the content of the capsule(s) with approximately 180 mL of Ensure® Plus liquid nutritional supplement [see Clinical Pharmacology (12.3)] at room temperature [between 20°C to 25°C (68°F to 77°F)].
- Promptly administer the mixture orally or through a nasogastric tube (French size 14 or 16) within 2 hours of preparation.
- If using a nasogastric tube, flush it with 60 mL of water after administering the mixture [see Clinical Pharmacology (12.3)].
- Discard the prepared dose if not given within 2 hours.

2.3 Monitoring for Safety

Obtain the following blood tests prior to starting treatment with INREBIC, periodically during treatment, and as clinically indicated [see Warnings and Precautions (5.1, 5.2, 5.4, 5.5)]:

- Thiamine (Vitamin B1) level
- Complete blood count with platelets
- Creatinine and BUN
- Hepatic panel
- Amylase and lipase

2.4 Dose Modifications with Concomitant Use of Strong CYP3A4 Inhibitors

Reduce INREBIC dose when administering with strong CYP3A4 inhibitors to 200 mg once daily.

In cases where coadministration with a strong CYP3A4 inhibitor is discontinued, INREBIC dosage should be increased to 300 mg once daily during the first two weeks after discontinuation of the CYP3A4 inhibitor, and then to 400 mg once daily thereafter as tolerated [see Drug Interactions (7.1)].

2.5 Dose Modifications for Severe Renal Impairment

Reduce INREBIC dose to 200 mg once daily in patients with severe renal impairment (creatinine clearance (CLcr) 15 mL/min to 29 mL/min as estimated by Cockcroft-Gault (C-G) equation).

2.6 Dose Modifications for Adverse Reactions

Modify dose for hematologic and nonhematologic adverse reactions per Table 1 and Table 2. Discontinue INREBIC in patients unable to tolerate a dose of 200 mg daily. See Warnings and Precautions for other mitigating strategies.

Table 1: Dose Modifications for Hematologic Adverse Reactions
Hematologic Adverse Reactions | Dose Reduction
Grade 4 Thrombocytopenia or Grade 3 Thrombocytopenia with active bleeding | Interrupt dose until resolved to Grade 2 or lower or baseline. Restart dose at 100 mg daily below the last given dose.
Grade 4 Neutropenia | Interrupt dose until resolved to Grade 2 or lower or baseline. Restart dose at 100 mg daily below the last given dose.

Consider dose reductions for patients who become transfusion-dependent during treatment with INREBIC.

Table 2: Dose Reductions for Nonhematologic Adverse Reactions
Nonhematologic Adverse Reactions | Dose Reduction
Grade 3 or higher Nausea, Vomiting, or Diarrhea not responding to supportive measures within 48 hours | Interrupt dose until resolved to Grade 1 or lower or baseline. Restart dose at 100 mg daily below the last given dose.
Grade 3 or higher ALT, AST, or Bilirubin | Interrupt dose until resolved to Grade 1 or lower or baseline. Restart dose at 100 mg daily below the last given dose. Monitor ALT, AST, and bilirubin (total and direct) more frequently following the dose reduction. If reoccurrence of a Grade 3 or higher elevation, discontinue treatment with INREBIC.
Grade 3 or higher Other Nonhematologic Toxicities | Interrupt dose until resolved to Grade 1 or lower or baseline. Restart dose at 100 mg daily below the last given dose.

2.7 Management of Thiamine Levels and Wernicke's Encephalopathy (WE)

Assess thiamine levels and nutritional status prior to starting INREBIC. Do not start INREBIC in patients with thiamine deficiency. However, if thiamine levels are low, replete thiamine prior to starting treatment. While on INREBIC treatment all patients should receive prophylaxis with daily 100 mg oral thiamine and should have thiamine levels assessed as clinically indicated. If Wernicke's encephalopathy is suspected, immediately discontinue treatment with INREBIC and initiate parenteral thiamine treatment. Monitor until symptoms resolve or improve and thiamine levels normalize [see Warnings and Precautions (5.1) and Adverse Reactions (6.1)].

3 DOSAGE FORMS AND STRENGTHS

Capsules: 100 mg, reddish brown, opaque size 0, printed with "FEDR 100 mg" in white ink.

4 CONTRAINDICATIONS

None.

5 WARNINGS AND PRECAUTIONS

5.1 Encephalopathy, Including Wernicke's

Serious and fatal encephalopathy, including Wernicke's encephalopathy, has occurred in INREBIC-treated patients. Serious cases were reported in 1.3% (8/608) of patients treated with INREBIC in clinical trials and 0.16% (1/608) of cases were fatal.

Wernicke's encephalopathy is a neurologic emergency resulting from thiamine (Vitamin B1) deficiency. Signs and symptoms of Wernicke's encephalopathy may include ataxia, mental status changes, and ophthalmoplegia (e.g., nystagmus, diplopia). Any change in mental status, confusion, or memory impairment should raise concern for potential encephalopathy, including Wernicke's, and prompt a full evaluation including a neurologic examination, assessment of thiamine levels, and imaging. Assess thiamine levels in all patients prior to starting INREBIC. Do not start INREBIC in patients with thiamine deficiency. However, if thiamine levels are low, replete thiamine prior to starting treatment. While on treatment all patients should receive prophylaxis with oral thiamine and should have thiamine levels assessed as clinically indicated. If encephalopathy is suspected, immediately discontinue INREBIC and initiate parenteral thiamine. Monitor until symptoms resolve or improve and thiamine levels normalize [see Dosage and Administration (2.7) and Adverse Reactions (6.1)].

5.2 Anemia and Thrombocytopenia

Treatment with INREBIC can cause anemia and thrombocytopenia.

Anemia

New or worsening Grade 3 anemia occurred in 34% of INREBIC-treated patients. The median time to onset of the first Grade 3 anemia was approximately 2 months, with 75% of cases occurring within 3 months. Mean hemoglobin levels reached nadir after 12 to 16 weeks with partial recovery and stabilization after 16 weeks. Red blood cell transfusions were received by 51% of INREBIC-treated patients and permanent discontinuation of INREBIC occurred due to anemia in 1% of patients. Consider dose reduction for patients who become red blood cell transfusion dependent [see Dosage and Administration (2.6)].

Thrombocytopenia

New or worsening Grade ≥3 thrombocytopenia during the randomized treatment period occurred in 12% of INREBIC-treated patients. The median time to onset of the first Grade 3 thrombocytopenia was approximately 1 month; with 75% of cases occurring within 4 months. Platelet transfusions were received by 3.1% of INREBIC-treated patients. Permanent discontinuation of treatment due to thrombocytopenia and bleeding that required clinical intervention both occurred in 2.1% of INREBIC-treated patients.

Obtain a complete blood count (CBC) at baseline, periodically during treatment, and as clinically indicated. For Grade 3 thrombocytopenia with active bleeding or Grade 4 thrombocytopenia, interrupt INREBIC until resolved to less than or equal to Grade 2 or baseline. Restart dose at 100 mg daily below the last given dose and monitor platelets as clinically indicated [see Dosage and Administration (2.6)].

5.3 Gastrointestinal Toxicity

Gastrointestinal toxicities are the most frequent adverse reactions in INREBIC-treated patients. During the randomized treatment period, diarrhea occurred in 66% of patients, nausea in 62% of patients, and vomiting in 39% of patients. Grade 3 diarrhea and vomiting occurred in 5% and 3.1% of patients, respectively. The median time to onset of any grade nausea, vomiting, and diarrhea was 1 day, with 75% of cases occurring within 2 weeks of treatment.

Consider providing appropriate prophylactic antiemetic therapy (e.g., 5-HT3 receptor antagonists) during INREBIC treatment. Treat diarrhea with antidiarrheal medications promptly at the first onset of symptoms. For Grade 3 or higher nausea, vomiting, or diarrhea not responsive to supportive measures within 48 hours, interrupt INREBIC until resolved to Grade 1 or less or baseline. Restart dose at 100 mg daily below the last given dose [see Dosage and Administration (2.6)]. Monitor thiamine levels and replete as needed.

5.4 Hepatic Toxicity

Elevations of ALT and AST (all grades) during the randomized treatment period occurred in 43% and 40%, respectively, with Grade 3 or 4 in 1% and 0%, respectively, of INREBIC-treated patients. The median time to onset of any grade transaminase elevation was approximately 1 month, with 75% of cases occurring within 3 months.

Monitor hepatic function at baseline, periodically during treatment, and as clinically indicated. For Grade 3 or higher ALT and/or AST elevations (greater than 5 × ULN), interrupt INREBIC dose until resolved to Grade 1 or less or to baseline. Restart dose at 100 mg daily below the last given dose. If reoccurrence of a Grade 3 or higher elevation of ALT/AST, discontinue treatment with INREBIC [see Dosage and Administration (2.6)].

5.5 Amylase and Lipase Elevation

Grade 3 or higher amylase and/or lipase elevations developed in 2% and 10%, respectively, of INREBIC-treated patients. The median time to onset of any grade amylase or lipase elevation was 15 days, with 75% of cases occurring within 1 month of starting treatment. One patient developed pancreatitis in the fedratinib clinical development program (n=608) and pancreatitis resolved with treatment discontinuation.

Monitor amylase and lipase at baseline, periodically during treatment, and as clinically indicated. For Grade 3 or higher amylase and/or lipase elevations, interrupt INREBIC until resolved to Grade 1 or less or to baseline. Restart dose at 100 mg daily below the last given dose [see Dosage and Administration (2.6)].

5.6 Uveitis

Uveitis has been observed in post-approval clinical studies with an overall incidence of 4% (11/251). Among patients with INREBIC-associated uveitis, more than half cases observed were in Japanese patients (55%; 6/11). INREBIC-associated uveitis is a late-onset adverse reaction, with the first episode occurring at a median of 14 months after starting treatment, with a range of 8 to 22 months. Recurrent uveitis was reported in some patients who continued INREBIC. The uveitis episodes varied in severity, with grade 1/2 in 60% of episodes, and grade 3/4 in 40% of episodes. Topical steroids were sufficient for treatment in 75% of episodes, and systemic steroids were required in 25% of episodes. Among the patients developing uveitis, INREBIC was discontinued due to uveitis in 27% of patients.

Advise patients on the risks of developing uveitis before starting INREBIC therapy. Common uveitis symptoms include eye pain, redness, photophobia, floaters, and decreased vision. In case of symptoms, prompt ophthalmologic evaluation is recommended.

5.7 Major Adverse Cardiac Events (MACE)

Another Janus Kinase (JAK)-inhibitor has increased the risk of MACE, including cardiovascular death, myocardial infarction, and stroke (compared to those treated with TNF blockers) in patients with rheumatoid arthritis, a condition for which INREBIC is not indicated.

Consider the benefits and risks for the individual patient prior to initiating or continuing therapy with INREBIC, particularly in patients who are current or past smokers and patients with other cardiovascular risk factors. Patients should be informed about the symptoms of serious cardiovascular events and the steps to take if they occur.

5.8 Thrombosis

Another JAK-inhibitor has increased the risk of thrombosis, including deep venous thrombosis, pulmonary embolism, and arterial thrombosis (compared to those treated with TNF blockers) in patients with rheumatoid arthritis, a condition for which INREBIC is not indicated. In patients with MF treated with INREBIC in clinical trials, the rates of thromboembolic events were similar in INREBIC and placebo treated patients.

Promptly evaluate and treat patients with symptoms of thrombosis.

5.9 Secondary Malignancies

Another JAK-inhibitor has increased the risk of lymphoma and other malignancies excluding nonmelanoma skin cancer (NMSC) (compared to those treated with TNF blockers) in patients with rheumatoid arthritis, a condition for which INREBIC is not indicated. Patients who are current or past smokers are at additional increased risk.

Consider the benefits and risks for the individual patient prior to initiating or continuing therapy with INREBIC, particularly in patients with a known malignancy (other than a successfully treated NMSC), patients who develop a malignancy, and patients who are current or past smokers.

6 ADVERSE REACTIONS

The following clinically significant adverse reactions are described elsewhere in the labeling:

- Encephalopathy, including Wernicke's [see Warnings and Precautions (5.1)]
- Anemia and Thrombocytopenia [see Warnings and Precautions (5.2)]
- Gastrointestinal Toxicity [see Warnings and Precautions (5.3)]
- Hepatic Toxicity [see Warnings and Precautions (5.4)]
- Amylase and Lipase Elevation [see Warnings and Precautions (5.5)]
- Uveitis [see Warnings and Precautions (5.6)]
- Major Adverse Cardiac Events [see Warnings and Precautions (5.7)]
- Thrombosis [see Warnings and Precautions (5.8)]
- Secondary Malignancies [see Warnings and Precautions (5.9)]

6.1 Clinical Trials Experience

Because clinical trials are conducted under widely varying conditions, adverse reaction rates observed in the clinical trials of a drug cannot be directly compared to rates in the clinical trials of another drug and may not reflect the rates observed in practice.

The data in the WARNINGS AND PRECAUTIONS Section 5.1 Encephalopathy, including Wernicke's, reflect exposure to INREBIC as a single agent in 608 patients who received more than one dose (ranging from 30 mg to 800 mg) in Studies JAKARTA, ARD11936, JAKARTA2, ARD12042, ARD12888, TED12037/TED12015, INT12497, and TES13519, of whom 459 were patients with myelofibrosis, including 97 patients previously treated with ruxolitinib. Among the 608 patients receiving INREBIC, the median drug exposure was 37 weeks and the median number of cycles initiated was 9 cycles. Fifty-nine percent of 608 patients were exposed for 6 months or longer and 39% were exposed for 12 months or longer.

Using the dataset described above, the most common adverse reactions in >20% of patients (N=608) were diarrhea, nausea, anemia, vomiting, fatigue, thrombocytopenia, and constipation.

JAKARTA Trial

The safety of INREBIC was evaluated in the randomized treatment period of the JAKARTA trial [see Clinical Studies (14)]. Key eligibility criteria included adult patients with intermediate-2 or high-risk primary MF or post-PV MF or post-ET MF with splenomegaly, platelet count ≥50 × 10^9/L, and no splenectomy. Patients received INREBIC at 400 mg daily (n=96) or placebo (n=95). Among patients receiving INREBIC, 82% were exposed for more than 6 months and 65% for more than one year. Patients had a median duration of exposure to INREBIC 400 mg daily of 15.5 months compared with placebo where patients were treated for 6 months or until disease progression after which patients were allowed to crossover to active treatment. The median age of patients who received INREBIC was 65 years (range: 27 to 86 years), 59% were male, 90% were White, 8% were Asian, 1% were Black, 1% were Other, and 92% had an Eastern Cooperative Oncology Group (ECOG) performance status of 0 to 1.

Serious adverse reactions occurred in 21% of INREBIC-treated patients. Serious adverse reactions in ≥2% of patients receiving INREBIC 400 mg daily included cardiac failure (5%) and anemia (2%). Fatal adverse reactions of cardiogenic shock occurred in 1% of patients receiving INREBIC 400 mg daily.

Permanent discontinuation due to an adverse reaction occurred in 14% of patients receiving INREBIC. Most frequent reasons for permanent discontinuation in ≥2% of patients receiving INREBIC included cardiac failure (3%), thrombocytopenia, myocardial ischemia, diarrhea, and increased blood creatinine (2% each).

Dosage interruptions due to an adverse reaction during the randomized treatment period occurred in 21% of patients who received INREBIC. Adverse reactions requiring dosage interruption in >3% of patients who received INREBIC included diarrhea and nausea.

Dosage reductions due to an adverse reaction during the randomized treatment period occurred in 19% of patients who received INREBIC. Adverse reactions requiring dosage reduction in >2% of patients who received INREBIC included anemia (6%), diarrhea (3%), vomiting (3%), and thrombocytopenia (2%).

The most common adverse reactions (reported in ≥20%) were diarrhea, nausea, anemia, and vomiting.

Tables 3 and 4 summarize the common adverse reactions and laboratory abnormalities, respectively, in JAKARTA during randomized treatment.

Table 3: Adverse Reactions Reported in ≥5% Patients Receiving INREBIC 400 mg with a Difference between Arms of >5% during Randomized Treatment
Adverse Reactiona | INREBIC 400 mg (n=96) |  | Placebo (n=95)
Adverse Reactiona | All Grades % | Grade ≥3b % | All Grades % | Grade ≥3 %
Diarrhea | 66 | 5 | 16 | 0
Nausea | 62 | 0 | 15 | 0
Anemia | 40 | 30 | 14 | 7
Vomiting | 39 | 3.1 | 5 | 0
Fatigue or asthenia | 19 | 5 | 16 | 1.1
Muscle spasms | 12 | 0 | 1.1 | 0
Blood creatinine increased | 10 | 1 | 1.1 | 0
Pain in extremity | 10 | 0 | 4.2 | 0
Alanine aminotransferase Increased | 9 | 0 | 1.1 | 0
Headache | 9 | 0 | 1.1 | 0
Weight increased | 9 | 0 | 4.2 | 0
Dizziness | 8 | 0 | 3.2 | 0
Bone pain | 8 | 0 | 2.1 | 0
Urinary tract infectionc | 6 | 0 | 1.1 | 0
Dysuria | 6 | 0 | 0 | 0
Aspartate aminotransferase increased | 5 | 0 | 1.1 | 0
a CTCAE version 4.03.
b Only 1 Grade 4 event (anemia).
c Includes cystitis.

Clinically significant adverse reactions reported in 5% or less of patients: hypertension of all grades was reported in 4.2% of patients and Grade 3 or higher in 3% of INREBIC-treated patients.

Changes in selected postbaseline laboratory values that were observed are shown in Table 4 for the JAKARTA trial during randomized treatment.

Table 4: Selected Laboratory Abnormalities That Have Worsened from Baseline (≥20%) in Patients Receiving INREBIC with a Difference between Arms of >10% When Compared to Placebo in JAKARTA during Randomized Treatment
 | INREBIC 400 mg (n=96) |  | Placebo (n=95)
Laboratory Parameter | All Grades % | Grade ≥3 % | All Grades % | Grade ≥3 %
Hematology
Anemia | 74 | 34 | 32 | 10
Thrombocytopenia | 47 | 12 | 26 | 10
Neutropenia | 23 | 5 | 13 | 3.3
Biochemistry
Creatinine increased | 59 | 3.1 | 19 | 1.1
ALT increased | 43 | 1 | 14 | 0
AST increased | 40 | 0 | 16 | 1.1
Lipase increased | 35 | 10 | 7 | 2.2
Hyponatremia | 26 | 5 | 11 | 4.3
Amylase increased | 24 | 2.1 | 5 | 0

In FEDR-MF-002, a randomized controlled post-marketing study of INREBIC (n=134) vs. best available therapy (BAT, n=67), the incidence of thiamine levels below the lower limit of normal (< 70 nmol/L) was 21% for INREBIC vs 5% for BAT. Thiamine levels < 30 nmol/L were not observed in the study. The median time to the first low thiamine level after initiation of INREBIC was 30 days. The frequency of low thiamine levels in participants receiving INREBIC was 2% in those receiving thiamine supplementation 100 mg orally per day vs. 39% in those not receiving thiamine supplementation.

6.2 Postmarketing Experience

The following adverse reactions have been identified during post approval use of INREBIC. Because these reactions are reported voluntarily from a population of uncertain size, it is not always possible to reliably estimate their frequency or establish a causal relationship to drug exposure.

Eye Disorders: Uveitis

7 DRUG INTERACTIONS

7.1 Effect of Other Drugs on INREBIC

Strong CYP3A4 Inhibitors

Coadministration of INREBIC with a strong CYP3A4 inhibitor increases fedratinib exposure [see Clinical Pharmacology (12.3)]. Increased exposure may increase the risk of adverse reactions. Consider alternative therapies that do not strongly inhibit CYP3A4 activity. Alternatively, reduce the dose of INREBIC when administering with a strong CYP3A4 inhibitor [see Dosage and Administration (2.4)].

Strong and Moderate CYP3A4 Inducers

Coadministration of INREBIC with a strong or moderate CYP3A4 inducer can decrease fedratinib exposure [see Clinical Pharmacology (12.3)]. Decreased exposure may reduce the effectiveness of INREBIC. Avoid INREBIC with strong and moderate CYP3A4 inducers.

Dual CYP3A4 and CYP2C19 Inhibitors

Coadministration of INREBIC with a dual CYP3A4 and CYP2C19 inhibitor increases fedratinib exposure [see Clinical Pharmacology (12.3)]. Increased exposure may increase the risk of adverse reactions. Due to potential increase of exposure, patients taking concomitant dual CYP3A4 and CYP2C19 inhibitors require more intensive safety monitoring and, if necessary, dose modifications of INREBIC based on adverse reactions [see Dosage and Administration (2.6)].

7.2 Effect of INREBIC on Other Drugs

CYP3A4, CYP2C19, or CYP2D6 Substrate Drugs

Coadministration of INREBIC with drugs that are CYP3A4 substrates, CYP2C19 substrates, or CYP2D6 substrates increases the concentrations of these drugs, which may increase the risk of adverse reactions of these drugs [see Clinical Pharmacology (12.3)]. Monitor for adverse reactions and adjust the dose of drugs that are CYP3A4, CYP2C19, or CYP2D6 substrates as necessary when coadministered with INREBIC.

OCT2 and MATE1/2-K Substrate Drugs

Coadministration of INREBIC with drugs that are renally excreted via organic cation transporter (OCT2) and multidrug and toxin extrusion (MATE)1/2-K can decrease renal clearance of those drugs [see Clinical Pharmacology (12.3)]. Monitor for adverse reactions and consider dose modifications for drugs that are renally excreted via OCT2 or MATE1/2-K (e.g., metformin), as necessary when coadministered with INREBIC.

8 USE IN SPECIFIC POPULATIONS

8.1 Pregnancy

Risk Summary

There are no available data on INREBIC use in pregnant women to evaluate for a drug-associated risk of major birth defects, miscarriage or adverse maternal or fetal outcomes. In animal reproduction studies, oral administration of fedratinib to pregnant rats during organogenesis at doses considerably lower than the recommended human daily dose of 400 mg/day resulted in adverse developmental outcomes (see Data). Consider the benefits and risks of INREBIC for the mother and possible risks to the fetus when prescribing INREBIC to a pregnant woman.

The background risk of major birth defects and miscarriage for the indicated population is unknown. Adverse outcomes in pregnancy occur regardless of the health of the mother or the use of medications. In the U.S. general population, the estimated background risk of major birth defects and miscarriage in clinically recognized pregnancies is 2% to 4% and 15% to 20%, respectively.

Data

Animal Data

In an embryo-fetal development study in pregnant rats, fedratinib administration at a dose of 30 mg/kg/day during organogenesis (gestation days 6 to 17) was associated with adverse developmental outcomes including skeletal variations (such as additional ossification center of neuronal arches). These effects occurred in rats at approximately 0.1 times the clinical exposure based on AUC at the recommended daily dose. At lower doses of 10 mg/kg/day (0.01 times the clinical exposure at the recommended daily dose), fedratinib administered to pregnant rats resulted in maternal toxicity of decreased gestational weight gain.

In an embryo-fetal development study in pregnant rabbits, fedratinib administration during organogenesis (gestation Days 6 to 18) did not produce developmental or maternal toxicity at doses up to the highest dose level tested, 30 mg/kg/day (approximately 0.08 times the clinical exposure at the recommended daily dose). In a separate study, administration of 80 mg/kg/day fedratinib to rabbits resulted in maternal mortality.

In a pre- and postnatal study in rats, fedratinib was administered to pregnant female rats at doses of 3, 10, or 30 mg/kg/day from Day 6 of gestation through Day 20 of lactation, with weaning on Day 21. A slight decrease in maternal body weight gain during gestation occurred at 30 mg/kg/day. The offspring from the high dose (30 mg/kg) had decreased body weight preweaning in both sexes and postweaning through the maturation phase in males. These effects occurred at exposures approximately 0.1 times the clinical exposure at the recommended daily dose.

8.2 Lactation

Risk Summary

There are no data on the presence of fedratinib or its metabolites in human milk, the effects on the breastfed child, or the effects on milk production. Because of the potential for serious adverse reactions in a breastfed child, advise patients not to breastfeed during treatment with INREBIC, and for at least 1 month after the last dose.

8.4 Pediatric Use

The safety and effectiveness of INREBIC in pediatric patients have not been established.

8.5 Geriatric Use

Of the total number of patients with myelofibrosis who received an INREBIC dose of 400 mg in the clinical studies, 47.3% were greater than 65 years of age and 12.3% were greater than 75 years of age. No overall differences in safety or effectiveness of INREBIC were observed between these patients and younger patients.

8.6 Renal Impairment

Reduce INREBIC dose when administered to patients with severe renal impairment (CLcr 15 mL/min to 29 mL/min by Cockcroft-Gault) [see Dosage and Administration (2.5) and Clinical Pharmacology (12.3)]. No modification of the starting dose is recommended for patients with mild to moderate renal impairment (CLcr 30 mL/min to 89 mL/min by Cockcroft-Gault). Due to potential increase of exposure, patients with preexisting moderate renal impairment require more intensive safety monitoring, and if necessary, dose modifications based on adverse reactions [see Dosage and Administration (2.6)].

10 OVERDOSAGE

Consider contacting the Poison Help line (1-800-222-1222) or a medical toxicologist for additional overdose management recommendations.

11 DESCRIPTION

INREBIC (fedratinib) is a kinase inhibitor with the chemical name N-tert-butyl-3-[(5-methyl-2-{[4-(2-pyrrolidin-1-ylethoxy)phenyl]amino}pyrimidin-4-yl)amino]benzenesulfonamide dihydrochloride monohydrate. Its empirical formula is C27H36N6O3S∙2HCl∙H2O and a molecular weight of 615.62. Fedratinib exhibits pH-dependent aqueous solubility; it is freely soluble in the acidic condition (>100 mg/mL at pH 1) and practically insoluble in the neutral condition (4 mcg/mL at pH 7.4). The chemical structure is:

INREBIC (fedratinib) is available as 100-mg (equivalent to 117.3 mg of fedratinib dihydrochloride monohydrate) hard gelatin capsules for oral administration. Each capsule contains inactive ingredients of silicified microcrystalline cellulose and sodium stearyl fumarate. The capsule shell contains gelatin, red iron oxide, titanium dioxide and white ink.

12 CLINICAL PHARMACOLOGY

12.1 Mechanism of Action

Fedratinib is an oral kinase inhibitor with activity against wild type and mutationally activated Janus Associated Kinase 2 (JAK2) and FMS-like tyrosine kinase 3 (FLT3). Fedratinib is a JAK2-selective inhibitor with higher inhibitory activity for JAK2 over family members JAK1, JAK3 and TYK2. Abnormal activation of JAK2 is associated with myeloproliferative neoplasms (MPNs), including myelofibrosis and polycythemia vera. In cell models expressing mutationally active JAK2V617F or FLT3ITD, fedratinib reduced phosphorylation of signal transducer and activator of transcription (STAT3/5) proteins, inhibited cell proliferation, and induced apoptotic cell death. In mouse models of JAK2V617F-driven myeloproliferative disease, fedratinib blocked phosphorylation of STAT3/5, and improved survival, white blood cell counts, hematocrit, splenomegaly, and fibrosis.

12.2 Pharmacodynamics

Fedratinib inhibited cytokine-induced STAT3 phosphorylation in whole blood from patients with myelofibrosis. The inhibition of STAT3 phosphorylation was maximal approximately 2 hours after the first dose, with values returning to near baseline at 24 hours. After daily administration of fedratinib, levels of inhibition at steady state PK were similar to the maximal inhibition reached after the first dose of 300 (0.75 times the recommended dose), 400 or 500 mg (1.25 times the recommended dose) of fedratinib.

Cardiac Electrophysiology

The potential for QTc prolongation with fedratinib was evaluated in 31 patients with solid tumors. No large mean increase in the QTc interval (>20 ms) was detected with daily dosing of fedratinib 500 mg (1.25 times the recommended dose) for 14 days.

12.3 Pharmacokinetics

INREBIC at 300 mg to 500 mg once daily (0.75 to 1.25 times the recommended dose) results in a dose proportional increase in geometric mean fedratinib peak concentrations (Cmax) and the area under the plasma concentration time curve over the dosing interval (AUCtau). The mean steady state levels are achieved within 15 days of daily dosing. The mean accumulation ratio ranged between 3- to 4-fold.

At the dose of 400 mg once daily, the geometric mean (coefficient of variation, %CV) fedratinib Cmax is 1804 ng/mL (49%) and AUCtau is 26870 ng.hr/mL (43%) in patients with myelofibrosis.

Absorption

Following 400 mg once daily, fedratinib median time to peak concentrations (Tmax) at steady-state is 3 hours (range: 2 to 4 hours).

Following the administration of a single 400 mg dose of fedratinib delivered orally or via nasogastric tube with contents from four 100-mg capsules dispersed in approximately 180 mL nutritional supplement (Ensure® Plus), the systemic exposures of fedratinib are similar.

Effect of Food

A low-fat, low-calorie (total 162 calories: 6% from fat, 78% from carbohydrate and 16% from protein) or a high-fat, high-calorie (total 815 calories: 52% from fat, 33% from carbohydrate and 15% from protein) meal increased area under the curve over time to infinity (AUCinf) up to 24% and Cmax up to 14% of a single 500 mg dose (1.25 times the recommended dose) of fedratinib.

Distribution

The apparent volume of distribution of fedratinib at steady-state is 1770 L in patients with myelofibrosis at 400 mg once daily dose. Fedratinib is 92% or greater bound to human plasma proteins.

Elimination

Fedratinib pharmacokinetics is characterized by a biphasic disposition with an effective half-life of 41 hours, a terminal half-life of approximately 114 hours, and apparent clearance (CL/F) (%CV) of 13 L/hr (51%) in patients with myelofibrosis.

Metabolism

Fedratinib is metabolized by CYP3A4, CYP2C19, and flavin-containing monooxygenase 3 (FMO3). Fedratinib accounts for approximately 80% of total circulating drug in plasma after oral administration.

Excretion

Following a single oral dose of radiolabeled fedratinib, 77% (23% unchanged) of the administered dose was excreted in feces and 5% (3% unchanged) was eliminated in urine.

Specific Populations

Age (20 years to 95 years), race (White, Asians), sex, body weight (40 kg to 135 kg), mild (Child-Pugh A), moderate (Child-Pugh B), or severe (Child-Pugh C) hepatic impairment, and mild (CLcr 60 mL/min to 89 mL/min by C-G) renal impairment did not have clinically meaningful effects on the pharmacokinetics of fedratinib.

Patients with Renal Impairment

Following a single 300 mg dose (0.75 times the recommended dose) of INREBIC, the AUCinf of fedratinib increased by 1.5-fold in subjects with moderate (CLcr 30 mL/min to 59 mL/min by C-G) renal impairment and 1.9-fold in subjects with severe (CLcr 15 mL/min to 29 mL/min by C-G) renal impairment, compared to that in subjects with normal renal function (CLcr ≥90 mL/min by C-G).

Drug Interaction Studies

Clinical Studies and Model-Informed Approaches

Effect of Strong and Moderate CYP3A4 Inhibitors

Coadministration of ketoconazole (strong CYP3A4 inhibitor: 200 mg twice daily) with a single dose of INREBIC (300 mg; 0.75 times the recommended dose) increased fedratinib AUCinf by 3-fold.

Coadministration of ketoconazole (400 mg once daily) with INREBIC 400 mg once daily is predicted to increase fedratinib AUC at steady state by 2-fold.

Coadministration of moderate CYP3A4 inhibitors, erythromycin (500 mg three times daily) or diltiazem (120 mg twice daily), with INREBIC 400 mg once daily is predicted to increase fedratinib AUC at steady state by 1.2-, and 1.1-fold, respectively.

Effect of Dual CYP3A4 and CYP2C19 Inhibitor

Coadministration of fluconazole (dual CYP3A4 and CYP2C19 inhibitor; 200 mg once daily) with a single dose of fedratinib (100 mg; 0.25 times the recommended dose) increased AUCinf by 1.7-fold.

Coadministration of fluconazole (200 mg once daily) with INREBIC 400 mg once daily is predicted to increase fedratinib AUC at steady state by approximately 1.5-fold.

Effect of Strong and Moderate CYP3A4 Inducers

Coadministration of rifampin (strong CYP3A4 inducer: 600 mg once daily) or efavirenz (moderate CYP3A4 inducer: 600 mg once daily) with a single dose of fedratinib (500 mg; 1.25 times the recommended dose) decreased AUCinf of fedratinib by approximately 81% or 47%, respectively.

Effect of Gastric Acid Reducing Agents

Coadministration of pantoprazole (proton pump inhibitor: 40 mg once daily) with a single dose of INREBIC (500 mg; 1.25 times the recommended dose) increased fedratinib AUCinf by 1.2-fold.

Effect of Fedratinib on Drugs that are CYP3A, CYP2C19, or CYP2D6 Substrates

Coadministration of a single dose of midazolam (CYP3A substrate: 2 mg), omeprazole (CYP2C19 substrate: 20 mg), and metoprolol (CYP2D6 substrate: 100 mg) with fedratinib increased midazolam, omeprazole, or metoprolol AUCinf by 4-, 3-, and 2-fold, respectively.

In Vitro and Clinical Transporter Studies

Fedratinib as a Substrate for Transporters:

Fedratinib is a substrate of P-glycoprotein (P-gp) but not breast cancer resistance protein (BCRP), BSEP, multidrug resistance protein (MRP2), and organic anion transporting polypeptide (OATP)1B1 and OATP1B3 in vitro.

Effect of Fedratinib on Transporter Substrates

Fedratinib inhibits P-gp, BCRP, OATP1B1, OATP1B3, OCT1, OCT2, MATE1, and MATE2-K, but not BSEP, MRP2, and organic anion transporter (OAT)1 and OAT3 in vitro.

Coadministration of a single dose of fedratinib (600 mg; 1.5 times the recommended dose) with a single dose of digoxin (P-gp substrate: 0.25 mg), rosuvastatin (OATP1B1/1B3 and BCRP substrate: 10 mg), and metformin (OCT2 and MATE1/2-K substrate: 1000 mg) had no clinically meaningful effect on the AUCinf of digoxin, rosuvastatin, and metformin. Renal clearance of metformin was decreased by 36% in the presence of fedratinib. Contrary to unchanged PK, the glucose lowering PD effect of metformin in the presence of fedratinib appears reduced, with baseline adjusted glucose AUC being approximately 50% higher in response to an oral glucose challenge.

13 NONCLINICAL TOXICOLOGY

13.1 Carcinogenesis, Mutagenesis, Impairment of Fertility

Fedratinib was not carcinogenic in the 6-month Tg.rasH2 transgenic mouse model.

Fedratinib was not mutagenic in a bacterial mutagenicity assay (Ames test) or clastogenic in in vitro chromosomal aberration assay (Chinese hamster ovary cells) or in vivo in a micronucleus test in rats.

In a fertility study in rats, fedratinib was administered for at least 70 days (males) and 14 days (females) prior to cohabitation and up to the implantation day (gestation day 7). Fedratinib had no effect on the estrous cycle parameters, mating performance, fertility, pregnancy rate or reproductive parameters in male or female rats at doses up to 30 mg/kg. The exposure (AUC) at the dose of 30 mg/kg/day is approximately 0.10 to 0.13 times the clinical exposure at the recommended daily dose.

13.2 Animal Toxicology and/or Pharmacology

The JAK/STAT pathway has been implicated in bone formation and metabolism, and its inhibition may cause bone abnormalities, e.g., in developing bone. There is currently no evidence of bone abnormalities in patients who received INREBIC.

14 CLINICAL STUDIES

JAKARTA

JAKARTA (NCT01437787) was a double-blind, randomized, placebo-controlled trial in patients with intermediate-2 or high-risk myelofibrosis, post-polycythemia vera myelofibrosis or post-essential thrombocythemia myelofibrosis with splenomegaly. A total of 289 patients were randomized to receive either INREBIC 500 mg (N=97), 400 mg (n=96) or placebo (n=96) once daily for at least 6 cycles. The median age was 65 years (range 27 to 86 years), 47% of patients were older than 65 years and 59% were male. Sixty-four percent (64%) of patients had primary MF, 26% had post-polycythemia vera MF, and 10% had post-essential thrombocythemia MF. Fifty-two percent (52%) of patients had intermediate-2 risk, and 48% had high-risk disease. The median baseline hemoglobin level was 10.2 g/dL. The median baseline platelet count was 214 × 10^9/L; 16% of patients had a platelet count <100 × 10^9/L and 84% of patients had a platelet count ≥100 × 10^9/L. Patients had a baseline median palpable spleen length of 15 cm. Patients had a baseline median spleen volume as measured by magnetic resonance imaging (MRI) or computed tomography (CT) of 2568 mL (range of 316 to 8244 mL) (the upper limit of normal is approximately 300 mL). Patients underwent MRI or CT spleen volume assessment (after the third and sixth cycle) with a follow-up scan 4 weeks after Cycle 6.

The efficacy of INREBIC in the treatment of patients with primary or secondary myelofibrosis was established based upon the proportion of patients achieving greater than or equal to a 35% reduction from baseline in spleen volume at the End of Cycle 6 as measured by MRI or CT with a follow-up scan 4 weeks later.

Efficacy analyses are presented in Table 5.

Table 5: Percent of Patients Achieving 35% or Greater Reduction from Baseline in Spleen Volume at the End of Cycle 6 in the Phase 3 Study, JAKARTA (ITT Population)
Spleen Response by MRI/CT at the End of Cycle 6 with a Follow-up Scan 4 Weeks Later | INREBIC 400 mg N=96 n (%) | Placebo N=96 n (%)
Number (%) of Patients with Spleen Volume Reduction by 35% or More | 35 (37) | 1 (1)
p-value | p<0.0001

Figure 1 shows the percent change in spleen volume from baseline for patients who have an evaluable MRI/CT at the End of Cycle 6.

Figure 1: Percent Change in Spleen Volume from Baseline at the End of Cycle 6 for Each Patient in the Phase 3 Study, JAKARTA

N*: Subjects with available percent change in spleen volume at EOC6.

Based on Kaplan-Meier estimates, the median duration of spleen response was 18.2 months for the INREBIC 400 mg group.

Additional outcomes included the proportion of patients with a 50% or greater reduction in Total Symptom Score from baseline to the End of Cycle 6 as measured by the modified Myelofibrosis Symptom Assessment Form (MFSAF) v2.0 diary.

The modified MFSAF v2.0 is a patient diary capturing the 6 core symptoms of MF: night sweats, itching, abdominal discomfort, early satiety, pain under ribs on left side, and bone or muscle pain. The modified MFSAF diary was completed daily during the week prior to Day 1 of each treatment cycle, and at the End of Cycle 6. Symptom scores ranged from 0 ("absent") to 10 ("worst imaginable"). These scores were added to create the Total Symptom Score, which has a maximum score of 60. At baseline, the mean Total Symptom Score was 17.95 in the 400 mg group and 15.45 in the placebo group.

The proportion of patients with a 50% or greater reduction in Total Symptom Score was 40% in the INREBIC 400 mg group and 9% in the placebo group (Table 6). Results are excluded for 22 patients: 6 patients with a baseline Total Symptom Score of zero (2 in the INREBIC 400 mg group and 4 in the placebo group) and 16 patients with missing baseline (5 in the INREBIC 400 mg group and 11 in the placebo group).

Table 6: Improvement in Total Symptom Score in Patients with Myelofibrosis in the Phase 3 Study, JAKARTA
 | INREBIC 400 mg (N=89) n (%) | Placebo (N=81) n (%)
Number (%) of Patients with 50% or Greater Reduction in Total Symptom Score at the End of Cycle 6 | 36 (40) | 7 (9)
p-value | p<0.0001

Figure 2 shows the percent change in Total Symptom Score from baseline at the End of Cycle 6 for each patient.

Figure 2: Percent Change from Baseline in Total Symptom Score at the End of Cycle 6 for Each Patient in the Phase 3 Study, JAKARTA

N*: Subjects with available percent change in Total Symptom Score at EOC6.

Figure 3 displays the proportion of patients with at least a 50% improvement in each of the individual symptoms that comprised the Total Symptom Score indicating that all 6 of the symptoms contributed to the higher Total Symptom Score response rate in the group treated with INREBIC.

Figure 3: Proportion of Patients Achieving 50% or Greater Reduction in Individual Symptom Scores at the End of Cycle 6 with Nonzero Baseline Scores

16 HOW SUPPLIED/STORAGE AND HANDLING

16.1 How Supplied

INREBIC (fedratinib) 100 mg capsules: Reddish brown, opaque, size 0 capsule, printed with "FEDR 100 mg" in white ink.

- Bottles of 120 capsules (NDC 59572-720-12)

16.2 Storage

Store below 30°C (86°F).

17 PATIENT COUNSELING INFORMATION

Advise the patient to read the FDA-approved patient labeling (Medication Guide).

Discuss the following with patients prior to and during treatment with INREBIC.

Encephalopathy, including Wernicke's

Advise patients that serious and fatal encephalopathy, including Wernicke's, has occurred in patients taking INREBIC. Wernicke's encephalopathy is a neurological emergency resulting from acute thiamine (Vitamin B1) deficiency. Advise patients of the need to monitor thiamine levels [see Dosage and Administration (2.1,2.3,2.7), and Warnings and Precautions (5.1)]. Instruct patients that they should receive prophylaxis with thiamine 100 mg orally daily while taking INREBIC [see Dosage and Administration (2.7)]. Advise patients to seek emergency medical attention for any change in mental status such as confusion, drowsiness or memory impairment, cerebellar abnormalities such as ataxia, and ophthalmic abnormalities such as diplopia and nystagmus. Advise patients to contact their healthcare provider right away if they experience nausea, vomiting, diarrhea, and weight loss unresponsive to treatment resulting in malnutrition and lower thiamine levels, which may lead to Wernicke's encephalopathy [see Boxed Warning and Warnings and Precautions (5.1)].

Anemia and Thrombocytopenia

Advise patients that INREBIC is associated with anemia and thrombocytopenia, and of the need to monitor complete blood counts before and during treatment [see Warnings and Precautions (5.2)].

Gastrointestinal Toxicity

Advise patients to contact their healthcare provider if they experience intractable diarrhea, nausea, or vomiting. Prescribers should advise patients of the potential complications of severe diarrhea, nausea, or vomiting [see Warnings and Precautions (5.3)].

Hepatic Toxicity

Advise patients that INREBIC may increase liver enzymes and of the need to monitor liver enzyme levels [see Warnings and Precautions (5.4)].

Amylase and Lipase Elevation

Advise patients that INREBIC may increase amylase and lipase and of the need to monitor amylase and lipase [see Warnings and Precautions (5.5)].

Uveitis

Advise patients that INREBIC can cause uveitis and to contact their healthcare provider if they experience any symptoms, including eye pain, redness, photophobia, floaters, and decreased vision [see Warnings and Precautions (5.6)].

Major Adverse Cardiac Events (MACE)

Advise patients that events of major adverse cardiac events (MACE) including myocardial infarction, stroke, and cardiovascular death, have been reported in clinical studies with another JAK-inhibitor used to treat rheumatoid arthritis, a condition for which INREBIC is not indicated. Advise patients, especially current or past smokers or patients with other cardiovascular risk factors, to be alert for the development of signs and symptoms of cardiovascular events [see Warnings and Precautions (5.6)].

Thrombosis

Advise patients that events of DVT and PE have been reported in clinical studies with another JAK-inhibitor used to treat rheumatoid arthritis, a condition for which INREBIC is not indicated. Advise patients to tell their healthcare provider if they develop any signs or symptoms of a DVT or PE [see Warnings and Precautions (5.7)].

Secondary Malignancies

Advise patients, especially current or past smokers and patients with a known secondary malignancy (other than a successfully treated NMSC), that lymphoma and other malignancies (excluding NMSC) have been reported in clinical studies with another JAK-inhibitor used to treat rheumatoid arthritis, a condition for which INREBIC is not indicated [see Warnings and Precautions (5.8)].

Lactation

Advise patients not to breastfeed during treatment with INREBIC and for at least 1 month after the final dose [see Use in Specific Populations (8.2)].

Missed Dose

Instruct patients that if they miss a dose of INREBIC, skip the dose and take it the next day and return to normal schedule [see Dosage and Administration (2.2)]. Warn patients not to take 2 doses to make up for the missed dose.

Administration Instructions

For patients who cannot swallow INREBIC capsules whole or those with a nasogastric tube, mix the content of the capsule(s) with approximately 180 mL of Ensure® Plus liquid nutritional supplement [see Clinical Pharmacology (12.3)] at room temperature [between 20°C to 25°C (68°F to 77°F)] in a glass container, then promptly take by mouth or give through a nasogastric tube (French size 14 or 16) within 2 hours of preparation. If using a nasogastric tube, flush it with 60 mL of water after administering the mixture [see Dosage and Administration (2.2.)].

Marketed by:
Bristol-Myers Squibb Company
Princeton, NJ 08543 USA

INREBIC® is a trademark of Impact Biomedicines, Inc., a Bristol Myers Squibb company.

INRPI.009/MG.007

MEDICATION GUIDE
INREBIC® (inn-REH-bik)
(fedratinib)
capsules, for oral use

What is the most important information I should know about INREBIC?
INREBIC may cause serious side effects, including:

- Encephalopathy (including Wernicke's encephalopathy). A serious and sometimes fatal neurological problem called encephalopathy (including Wernicke's encephalopathy) has happened in some people who take INREBIC.
  Wernicke’s encephalopathy is a neurologic emergency that can happen if you do not have enough Vitamin B1 (thiamine) in your body. Your healthcare provider will do a blood test to check your Vitamin B1 level and treat you with Vitamin B1 if your level is too low before starting treatment with INREBIC. Your healthcare provider may also check your Vitamin B1 level during treatment with INREBIC. You should take a Vitamin B1 supplement (100 mg of thiamine) daily during treatment with INREBIC.
  Your healthcare provider may tell you to stop taking INREBIC if you develop side effects during treatment with INREBIC.
  Get emergency medical help right away if you develop the following:
  - confusion, memory problems or drowsiness
  - problems with balance and movement, such as difficulty walking
  - eye problems, such as double or blurred vision or abnormal eye movements
Call your healthcare provider right away if you experience diarrhea, nausea, vomiting, and weight loss that does not get better with treatment.

See “What are the possible side effects of INREBIC” for more information about side effects.

What is INREBIC?
INREBIC is a prescription medicine used to treat adults with certain types of myelofibrosis (MF).
It is not known if INREBIC is safe and effective in children.

Before taking INREBIC, tell your healthcare provider about all your medical conditions, including if you:

- have low Vitamin B1 (thiamine) levels
- have low red blood cell or platelet counts
- have or have had liver problems
- have or have had kidney problems
- are a current or past smoker
- have had a blood clot, heart attack, other heart problems, or stroke
- have or have had any other cancer
- are pregnant or plan to become pregnant. It is not known if INREBIC may harm your unborn baby.
- are breastfeeding or plan to breastfeed. It is not known if INREBIC passes into your breast milk. You should not breastfeed during treatment with INREBIC and for at least 1 month after your last dose. Talk to your healthcare provider about the best way to feed your baby during treatment with INREBIC.

Tell your healthcare provider about all the medicines you take, including prescription and over-the-counter medicines, vitamins, and herbal supplements.
Taking INREBIC with certain other medicines may cause side effects from INREBIC or from the other medicine and may affect the way that INREBIC works. Know the medicines you take. Keep a list of them to show your healthcare provider and pharmacist when you get a new medicine.

How should I take INREBIC?

- Take INREBIC exactly as your healthcare provider tells you to. Do not change your dose or stop taking INREBIC unless your healthcare provider tells you to.
- Your healthcare provider may change your dose, temporarily stop, or permanently stop treatment with INREBIC if you develop side effects.
- Take INREBIC 1 time each day.
- Take INREBIC with or without food. Taking INREBIC with a high fat meal may help to reduce nausea and vomiting symptoms.
- Take Vitamin B1 (thiamine 100 mg) by mouth daily to prevent low Vitamin B1 levels during treatment with INREBIC.
- If you miss a dose of INREBIC, skip the missed dose and take your usual dose the next day at your regularly scheduled time. Do not take 2 doses to make up for the missed dose.
- If you cannot swallow INREBIC capsules whole or have a nasogastric tube, the capsules can be opened, and the contents can be mixed with Ensure® Plus liquid nutritional supplement:
- Carefully open your prescribed dose of INREBIC capsules into a glass container and mix it with about 180 mL (6 oz) of liquid nutritional supplement at room temperature, between 68°F to 77°F (20°C to 25°C).
- Swallow the mixture right away or give it through a nasogastric (NG) tube (French size 14 or 16) within 2 hours of preparation. If using a NG tube, flush the NG tube with 60 mL (2 oz) of water after giving the INREBIC mixture.
- Throw away prepared dose if not given within 2 hours and mix a new dose.
- If you take too much INREBIC, call your healthcare provider or the Poison Help line at 1-800-222-1222 or go to the nearest hospital emergency room right away.

What are the possible side effects of INREBIC?
INREBIC may cause serious side effects, including:

- See "What is the most important information I should know about INREBIC?"
- Low blood cell counts. INREBIC may cause new or worsening low red blood cell counts (anemia) and low platelet counts (thrombocytopenia) in some people. You may need a blood transfusion if your blood counts drop too low. Your healthcare provider will do blood tests to check your blood counts before you start and during treatment with INREBIC. Tell your healthcare provider if you develop any bleeding or bruising during treatment with INREBIC.
- Diarrhea, nausea, and vomiting. Your healthcare provider may give you certain medicines to help treat your diarrhea, nausea, and vomiting. Call your healthcare provider or get emergency medical help right away if you have diarrhea, nausea, or vomiting that does not get better with treatment.
- Liver problems. INREBIC may cause increased liver enzymes. Your healthcare provider will do blood tests to check your liver function before starting and during treatment with INREBIC.
- Amylase and lipase increase. You may have increases in your blood amylase or lipase levels that may indicate a problem with your pancreas. Your healthcare provider will do blood tests to check your amylase or lipase levels before starting and during treatment with INREBIC.
- Eye problem called uveitis. INREBIC may cause inflammation of the middle layer of the eyeball (uvea) called uveitis. Tell your healthcare provider if you develop any symptoms, including eye pain, redness, sensitivity to light, new or increased floaters (specks or threads that float in your vision), or decrease in your vision. You may need to see an eye specialist to check your eyes if you develop any signs and symptoms of eye problems.
- Major cardiac events such as heart attack, stroke, or death. An increased risk of major cardiac events has happened in people, especially those who have cardiovascular risk factors and who are current or past smokers, while taking another Janus Kinase (JAK)-inhibitor to treat rheumatoid arthritis.
  Get emergency help right away if you get any symptoms of a heart attack or stroke during treatment with INREBIC, including:
  - discomfort in the center of your chest that lasts for more than a few minutes, or that goes away and comes back
  - severe tightness, pain, pressure, or heaviness in your chest, throat, neck, or jaw
  - pain or discomfort in your arms, back, neck, jaw, or stomach
  - shortness of breath with or without chest discomfort
  - breaking out in a cold sweat
  - nausea or vomiting
  - feeling lightheaded
  - weakness in one part or on one side of your body
  - slurred speech
- Blood clots. Increased risk of blood clots in the veins of the legs (deep vein thrombosis [DVT]) or lungs (pulmonary embolism [PE]) have happened in people taking another JAK-inhibitor for rheumatoid arthritis and may be life-threatening.
  Tell your healthcare provider right away if you have any signs and symptoms of blood clots during treatment with INREBIC, including:
  - swelling, pain, or tenderness in one or both legs
  - sudden unexplained chest or upper back pain
  - shortness of breath or difficulty breathing
- New (secondary) cancers. People who take another JAK-inhibitor for rheumatoid arthritis have an increased risk of new (secondary) cancers, including lymphoma and other cancers, except nonmelanoma skin cancer. People who smoke or who smoked in the past have an added increased risk of new cancers.

The most common side effects of INREBIC include:

- diarrhea
- nausea
- low red blood cell counts (anemia)
- vomiting

These are not all of the possible side effects of INREBIC.
Call your doctor for medical advice about side effects. You may report side effects to FDA at 1-800-FDA-1088.

How should I store INREBIC?

- Store INREBIC below 86°F (30°C).

Keep INREBIC and all medicines out of the reach of children.

General information about the safe and effective use of INREBIC.
Medicines are sometimes prescribed for purposes other than those listed in a Medication Guide. Do not use INREBIC for conditions for which it was not prescribed. Do not give INREBIC to other people, even if they have the same symptoms that you have. It may harm them. You can ask your pharmacist or healthcare provider for information about INREBIC that is written for health professionals.

What are the ingredients in INREBIC?
Active ingredient: fedratinib
Inactive ingredients: silicified microcrystalline cellulose and sodium stearyl fumarate. The capsule shell contains gelatin, red iron oxide, titanium dioxide and white ink.
Marketed by:
Bristol-Myers Squibb Company, Princeton, NJ 08543 USA
INREBIC® is a trademark of Impact Biomedicines, Inc., a Bristol Myers Squibb company.
INRMG.007 5/2025
For more information go to www.INREBIC.com or call 1-800-721-5072.

This Medication Guide has been approved by the U.S. Food and Drug Administration.
Revised: 5/2025

PRINCIPAL DISPLAY PANEL - 100 mg Capsule Bottle Label

NDC 59572-720-12

INREBIC®
(fedratinib) capsules

100 mg

Dispense the accompanying Medication Guide to each patient.

Rx only
120 Capsules